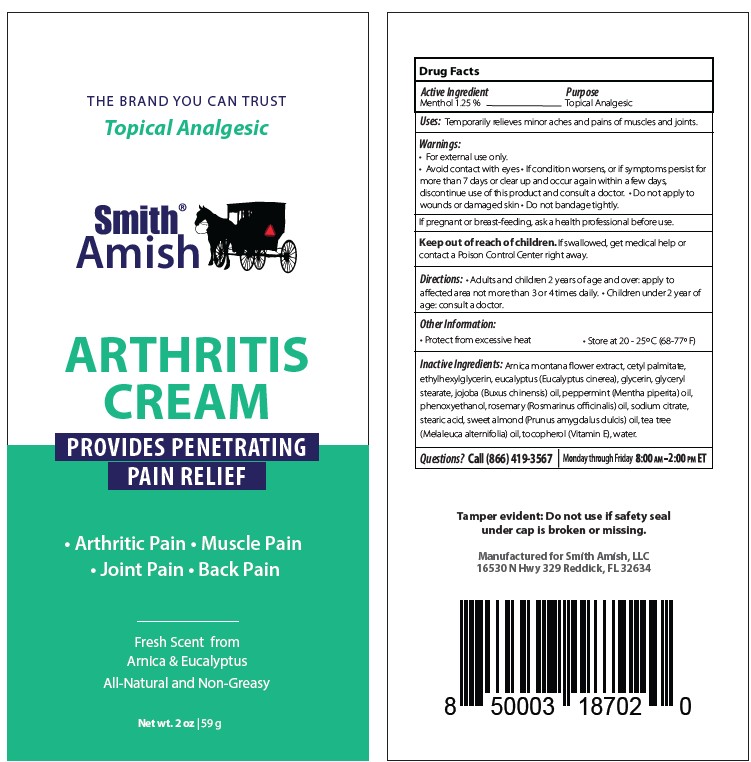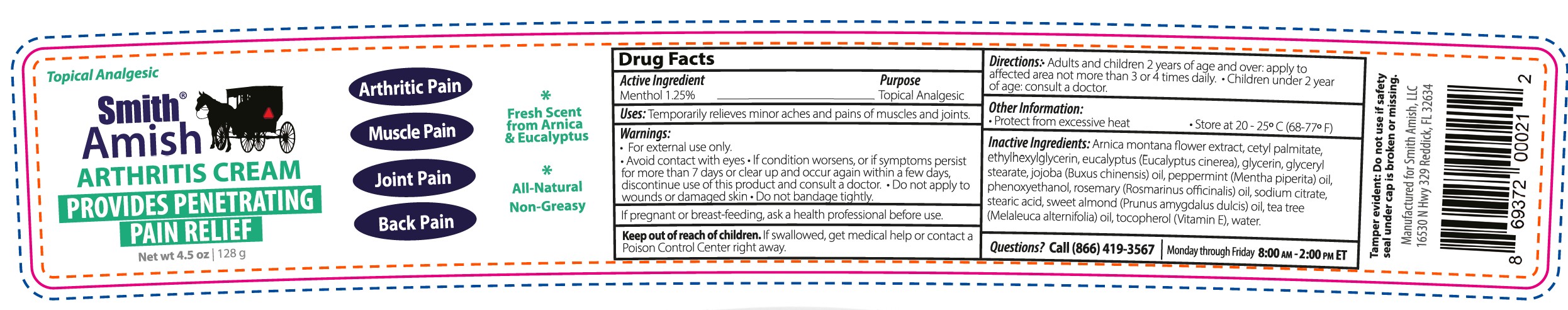 DRUG LABEL: ARTHRITIS
NDC: 72609-702 | Form: CREAM
Manufacturer: Smith Amish, LLC
Category: otc | Type: HUMAN OTC DRUG LABEL
Date: 20251212

ACTIVE INGREDIENTS: MENTHOL 1.25 g/100 g
INACTIVE INGREDIENTS: ALMOND OIL; JOJOBA OIL; SODIUM CITRATE; GLYCERYL MONOSTEARATE; PEPPERMINT OIL; .ALPHA.-TOCOPHEROL; ARNICA MONTANA WHOLE; CETYL PALMITATE; STEARIC ACID; TEA TREE OIL; WATER; ROSEMARY OIL; PHENOXYETHANOL; EUCALYPTUS OIL; GLYCERIN

Smith Amish Arthritis Cream (2oz) - 72609-702-02

Drug Facts Active Ingredient

Menthol 1.25%

Purpose

Topical analgesic

Uses

Temporarily relieves minor aches and pains of muscles and joints.

Warnings

- For external use only
- Avoid contact with eyes

STOP USE

- If condition worsens, or if symptoms persist for more than 7 days or cler up and occur again within a few days,, discontinue use of this product and consult a doctor.

PREGNANCY OR BREAST FEEDING

If pregnant or breast-feeding, ask a health professional before use.

Keep out of reach of children.

If swallowed, get medical help or contact a Poison Control Center right away.

Directions

Adults and children 2 years of age and over: apply to affected area not more than 3 to 4 times daily. Children under 2 years of age consult a doctor.

Other information

Protect from excessive heat

Store at 20-25oC (68-77F)

Inactive Ingredients

Arnica montana flower extract, cetyl palmitate, ethylhexylglycerin, eucalyptus (Eucalyptus cinerea), glycerin, glyceryl stearate, jojoba (Buxus chinensis) oil, peppermint (mentha piperita) oil, phenoxyethanol, rosemary (Rosmariunus officinalis) oil, sodium citrate, stearic acid, sweet almond (Prunus amydgalus dulcis) oil, tea tree (Melaleuca alternifolia) oil, tocopherol (Vitamin E), water

Questions?

Call (866) 419-3567

Monday through Friday 8:00am - 2:00pm ET

Tamper evident: Do not use if safety seal under cap is broken or missing.

Manufactured for Smith Amish LLC 16350 N Hwy 329 Reddick, FL 32634

Label

Smith Amish Arthritis Cream (72609-702-02)

Provides Penetrating Relief

- Arthritic pain
- Muscle Pain
- Joint Pain
- Back Pain

Fresh scent from Arnica & Eucalyptus

All natural and non-greasy

Net wt. 2oz (59g)

Smith Amish Arthritis Cream (72609-702-02)